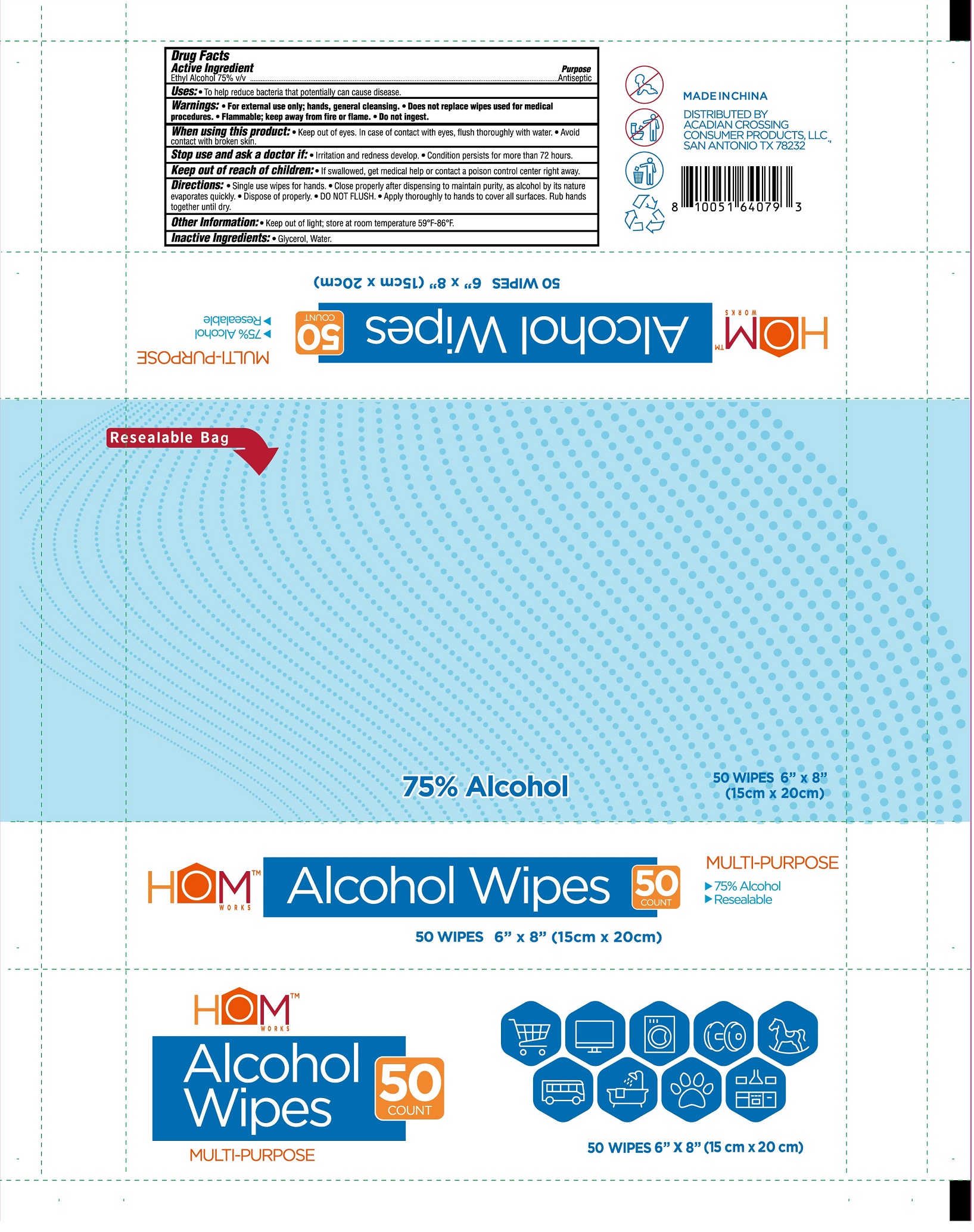 DRUG LABEL: Alcohol Wipes
NDC: 77412-199 | Form: PATCH
Manufacturer: Shandong Liaocheng Chaoyue Daily Necessities Co., Ltd.
Category: otc | Type: HUMAN OTC DRUG LABEL
Date: 20250930

ACTIVE INGREDIENTS: ALCOHOL 75 mL/100 mL
INACTIVE INGREDIENTS: water

Active Ingredient

Ethyl Alcohol 75% v/v

Purpose

Antiseptic

use

To help reduce bacteria that potentially can cause disease

Warnings

For external use only; hands, general cleansing.
Does not replace wipes used for medical procedures.
Flammable； keep away from fire or flame.
Do not ingest.

When using this product:

Keep out of eyes. In case of contact with eyes, flush thoroughly with water.

Avoid contact with broken skin.

Stop use and ask a doctor if

lrritation and redness develop.

Condition persists for more than 72 hours.

Keep out ofreach of children

If swallowed, get medical help or contact a poison control center right away.

Directions:

Single use wipes for hands.

Close properly after dispensing to maintain purity,as alcohol by its nature evaporates quickly.

Dispose of properly.

DO NOT FLUSH.

Apply thoroughly to hands to cover all surfaces. Rub hands together until dry.

Other Information

Keep out of light; store at room temperature 59°F-86°F

Inactive ingredients:

Glycerol, Water.